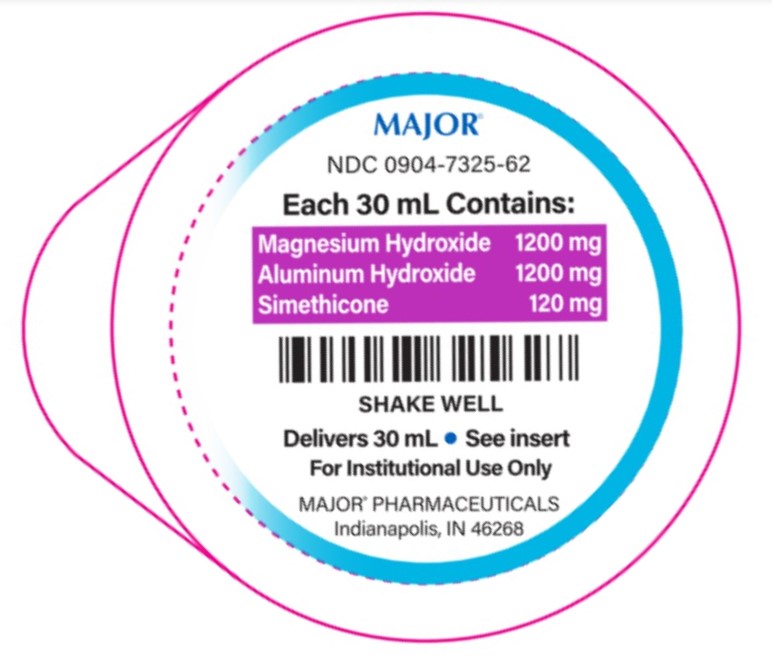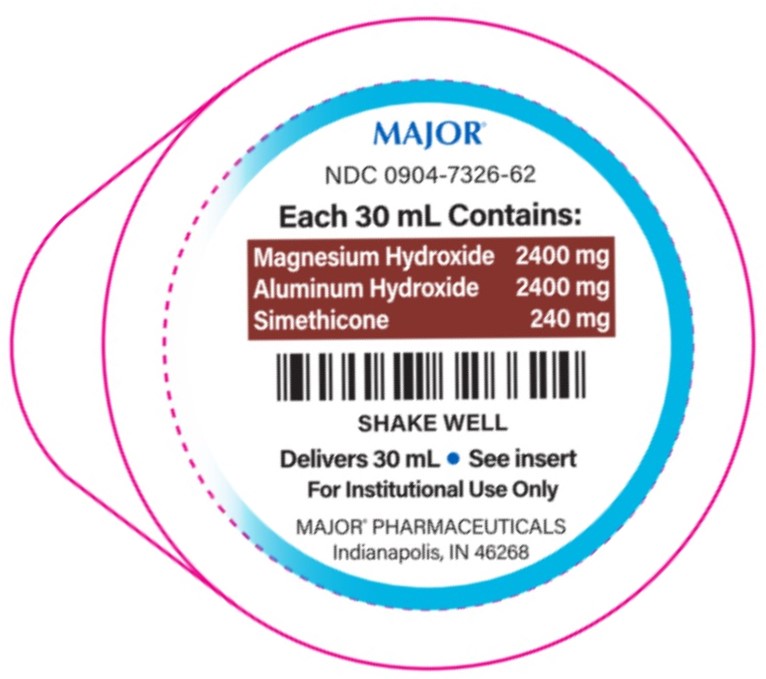 DRUG LABEL: Aluminum Hydroxide, Magnesium Hydroxide and Simethicone Suspension
NDC: 0904-7325 | Form: SUSPENSION
Manufacturer: Major Pharmaceuticals
Category: otc | Type: HUMAN OTC DRUG LABEL
Date: 20250904

ACTIVE INGREDIENTS: ALUMINUM HYDROXIDE 1200 mg/30 mL; MAGNESIUM HYDROXIDE 1200 mg/30 mL; DIMETHICONE, UNSPECIFIED 120 mg/30 mL
INACTIVE INGREDIENTS: BENZYL ALCOHOL; BUTYLPARABEN; CARBOXYMETHYLCELLULOSE SODIUM, UNSPECIFIED; HYPROMELLOSE, UNSPECIFIED; MICROCRYSTALLINE CELLULOSE; PROPYLPARABEN; WATER; SACCHARIN SODIUM; SORBITOL SOLUTION

Magnesium Hydroxide, Aluminum Hydroxide and Simethicone Suspension 1,200-1,200-120 mg/30 mL,
Magnesium Hydroxide, Aluminum Hydroxide and Simethicone Suspension Maximum Strength 2,400-2,400-240 mg/30 mL

Drug Facts

ACTIVE INGREDIENT

PURPOSE

1,200-1,200-120 mg/30 mL

Active ingredients (in each 30 mL) Purpose

Aluminum hydroxide 1,200 mg (equivalent to dried gel, USP)..............Antacid
Magnesium hydroxide 1,200 mg......................................................Antacid
Simethicone 120 mg......................................................................Antigas

2,400-2,400-240 mg/30 mL

Active ingredient (in each 30 mL) Purpose
Aluminum hydroxide 2,400 mg (equivalent to dried gel, USP)..............Antacid
Magnesium hydroxide 2,400 mg......................................................Antacid
Simethicone 240 mg......................................................................Antigas

INDICATIONS AND USAGE

Usesrelieves • heartburn • sour stomach • acid indigestion • the symptoms referred to as gas

Warnings

Ask a doctor before use if you have• kidney disease • a magnesium restricted diet

Ask a doctor or pharmacist before use if you aretaking another medication. This product may interact with certain medications.

Stop use and ask a doctor ifsymptoms last more than 2 weeks

PREGNANCY OR BREAST FEEDING

If pregnant or breast-feeding,ask a health professional before use.

Keep out of reach of children.

Directions • shake well before use

1,200-1,200-120 mg/30 mL

age | dose
Adults and children 12 years and older | 30mL, not more than 120 mL in 24 hrs
Children under 6 years of age | Do not use unless directed by a doctor

2,400-2,400-240 mg/30 mL

age | dose
Adults and children 12 years and older | 30mL, not more than 60 mL in 24 hrs
Children under 6 years of age | Do not use unless directed by a doctor

Other information

1,200-1,200-120 mg/30 mL

- each 30 mL containsmagnesium 510 mg and sodium 18 mg
- protect from freezing
- store at 20° to 25°C (68° to 77°F).
- do not use if lid seal is open or damaged
- retain this insert for full product information

2,400-2,400-240 mg/30 mL

- each 30 mL containsmagnesium 990 mg, sodium 30 mg
- store at 20° to 25°C (68° to 77°F).
- protect from freezing
- do not use if lid seal is open or damaged
- retain this insert for full product information

INACTIVE INGREDIENT

Inactive ingredientsbenzyl alcohol, butylparaben, carboxy-methycellulose sodium, flavor, hypromellose, microcrystalline cellulose, propylparaben, purified water, saccharin sodium, sorbitol solution

Questions or comments?(855) 879-4368

Distributed by:
MAJOR® PHARMACEUTICALS
Indianapolis, IN 46268

(800) 616-2471

Rev. 06/23

PACKAGE LABEL.PRINCIPAL DISPLAY PANEL

MAJOR®

NDC 0904-7325-62

Each 30 mL Contains:

Magnesium hydroxide 1,200 mg

Aluminum hydroxide 1,200 mg

Simethicone 120 mg

SHAKE WELL

Delivers 30 mL • See insert

For Institutional Use Only

MAJOR® PHARMACEUTICALS

Indianapolis, IN 46268

PACKAGE LABEL.PRINCIPAL DISPLAY PANEL

MAJOR®

NDC 0904-7326-62

Each 30 mL Contains:

Magnesium hydroxide 2,400 mg

Aluminum hydroxide 2,400 mg

Simethicone 240 mg

SHAKE WELL

Delivers 30 mL • See insert

For Institutional Use Only

MAJOR® PHARMACEUTICALS

Indianapolis, IN 46268